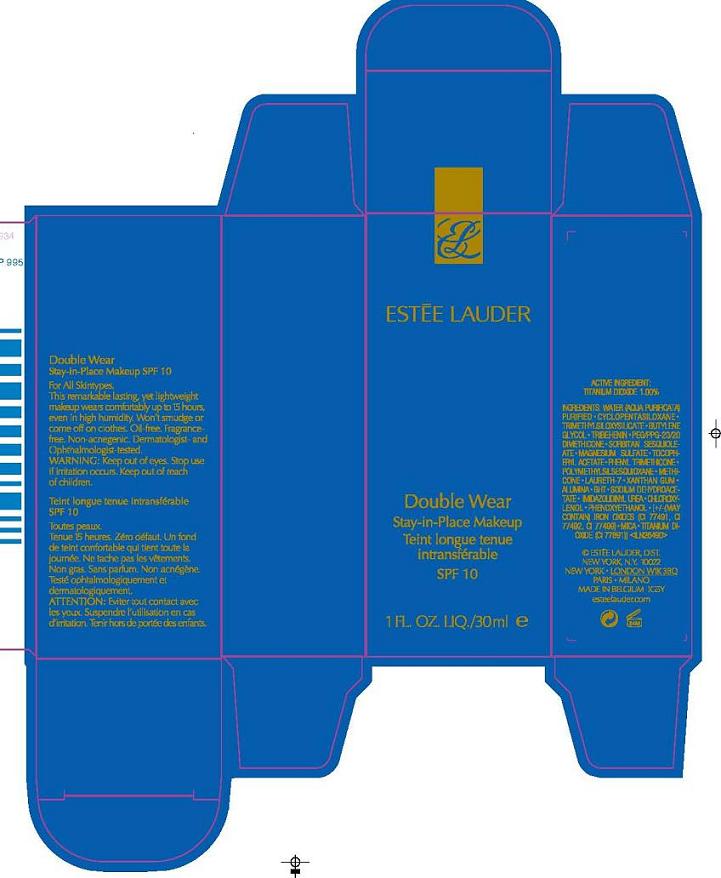 DRUG LABEL: DOUBLE WEAR 
NDC: 11559-945 | Form: LIQUID
Manufacturer: ESTEE LAUDER INC.
Category: otc | Type: HUMAN OTC DRUG LABEL
Date: 20100429

ACTIVE INGREDIENTS: TITANIUM DIOXIDE 1.0 mL/100 mL

ACTIVE INGREDIENT: TITANIUM DIOXIDE 1%

WARNINGS

WARNING: KEEP OUT OF EYES. STOP USE IF IRRITATION OCCURS. KEEP OUT OF REACH OF CHILDREN

PACKAGE LABEL

PRINCIPAL DISPLAY PANEL:

ESTEE LAUDER

DOUBLE WEAR

STAY-IN-PLACE MAKEUP

SPF 10

1 FL OZ LIQ/30 ML

ESTEE LAUDER DISTR.

NEW YORK, NY 10022